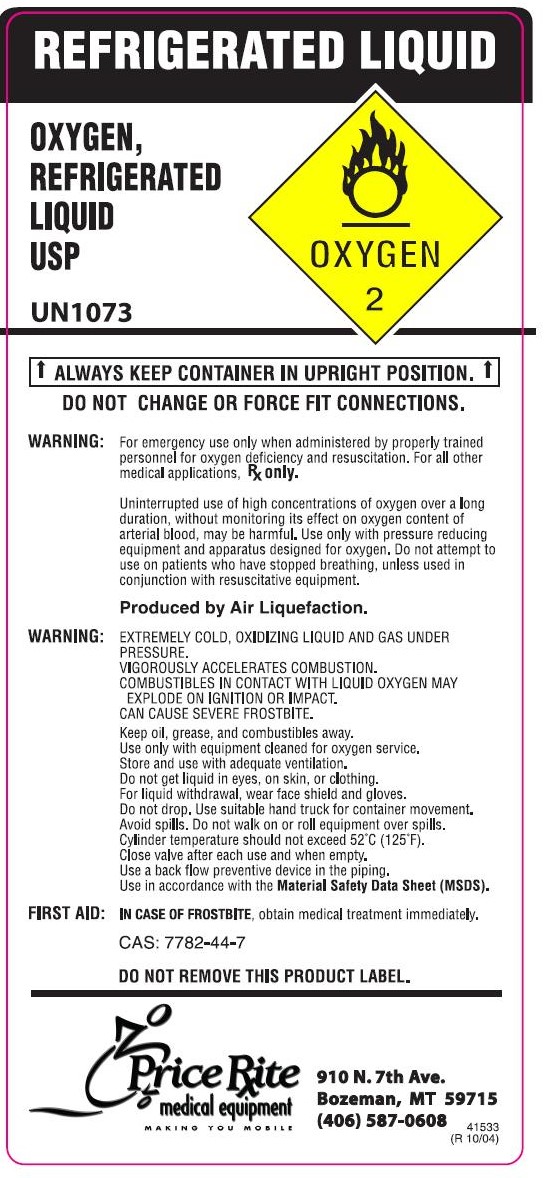 DRUG LABEL: Oxygen
NDC: 68540-001 | Form: GAS
Manufacturer: Price Rite Medical Equipment, Inc.
Category: prescription | Type: HUMAN PRESCRIPTION DRUG LABEL
Date: 20241111

ACTIVE INGREDIENTS: OXYGEN 990 mL/1 L

Oxygen Liquid Label

PACKAGE LABEL

REFRIGERATED LIQUID
OXYGEN, REFRIGERATED LIQUID USP UN1073 OXYGEN 2
ALWAYS KEEP CONTAINER IN UPRIGHT POSITION. DO NOT CHANGE OR FORCE FIT CONNECTIONS.
WARNING: For emergency use only when administered by properly trained personnel for oxygen deficiency and resuscitation. For all other medical applications, Rx ONLY. Uninterrupted use of high concentrations of oxygen over a long duration, without monitoring its effect on oxygen content of arterial blood, may be harmful. Use only with pressure reducing equipment and apparatus designed for use with oxygen. Do not attempt to use on patients who have stopped breathing unless used in conjunction with resuscitative equipment. Produced by Air Liquefaction.
WARNING: EXTREMELY COLD, OXIDIZING LIQUID AND GAS UNDER PRESSURE . VIGOROUSLY ACCELERATES COMBUSTION. COMBUSTIBLES IN CONTACT WITH LIQUID OXYGEN MAY EXPLODE ON IGNITION OR IMPACT. CAN CAUSE SEVERE FROSTBITE.
Keep oil, grease and combustibles away. Use only with equipment cleaned for oxygen. Store and use with adequate ventilation. Do not get liquid in eyes, on skin, or clothing. For liquid withdrawal, wear face shield and gloves. Do not drop. Use suitable hand truck for container movement. Avoid spills. O not walk on or roll equipment over spills. Cylinder temperature should not exceed 52 C (125F). Close valve after each use and when empty. Use a back flow preventive device in the piping. Use in accordance with Material Safety Data Sheet (MSDS). FIRST AID : IN CASE OF FROSTBITE, obtain medical treatment immediately.
CAS: 7782-44-7
DO NOT REMOVE THIS PRODUCT LABEL.
Price Rite medical equipment MAKING YOU MOBILE 910 N. 7th Ave. Bozeman, MT 59715 (406) 587-0608
41533 (R 10/04)